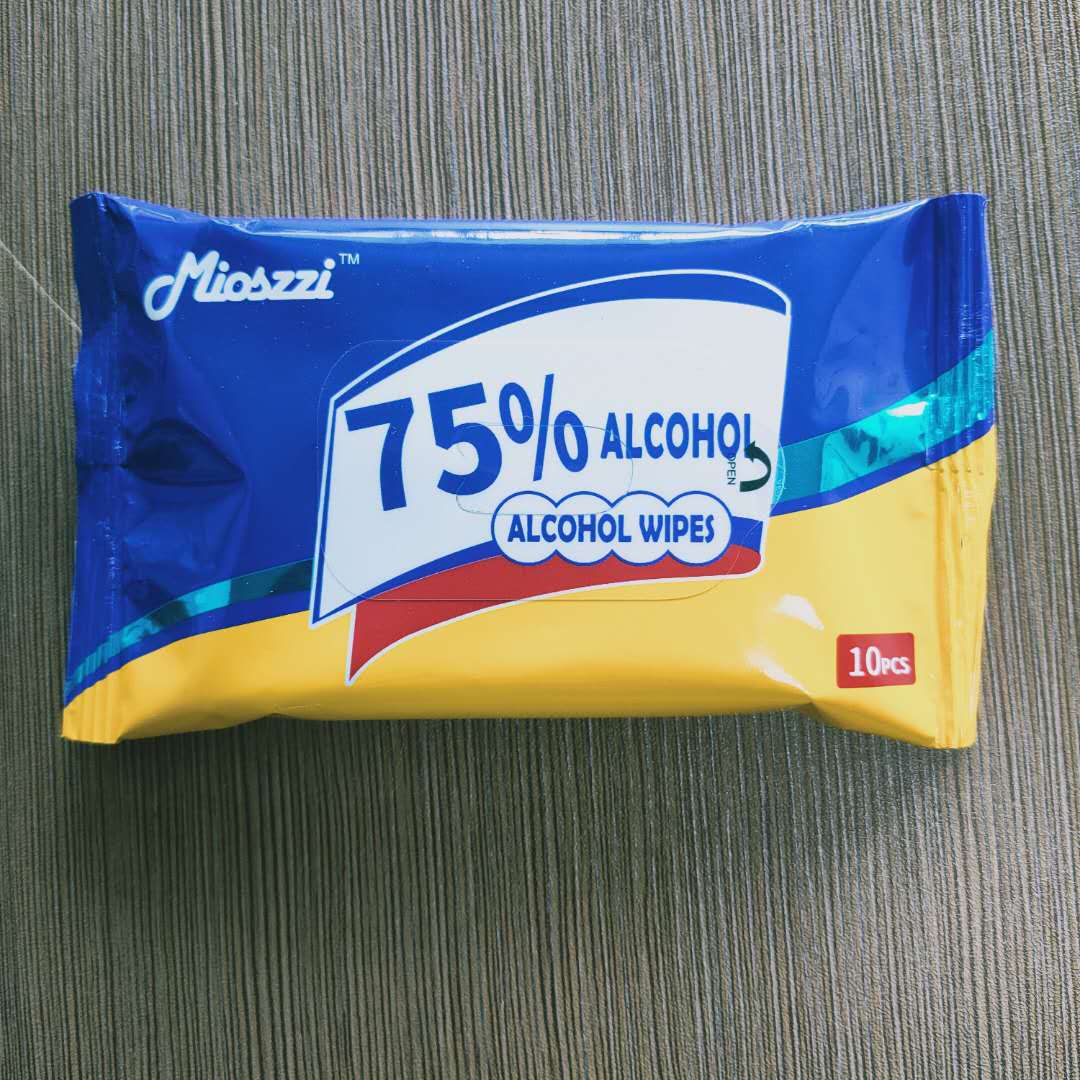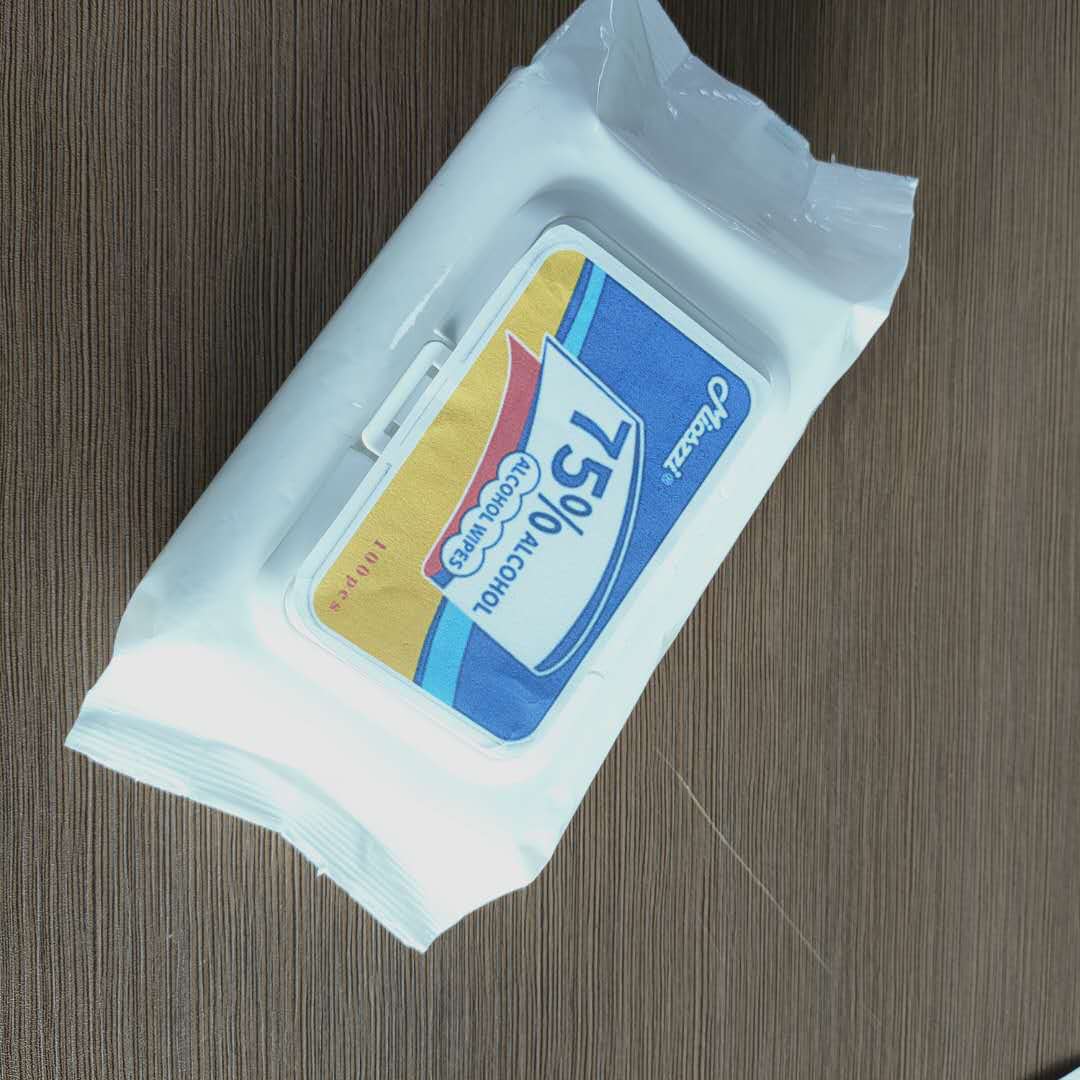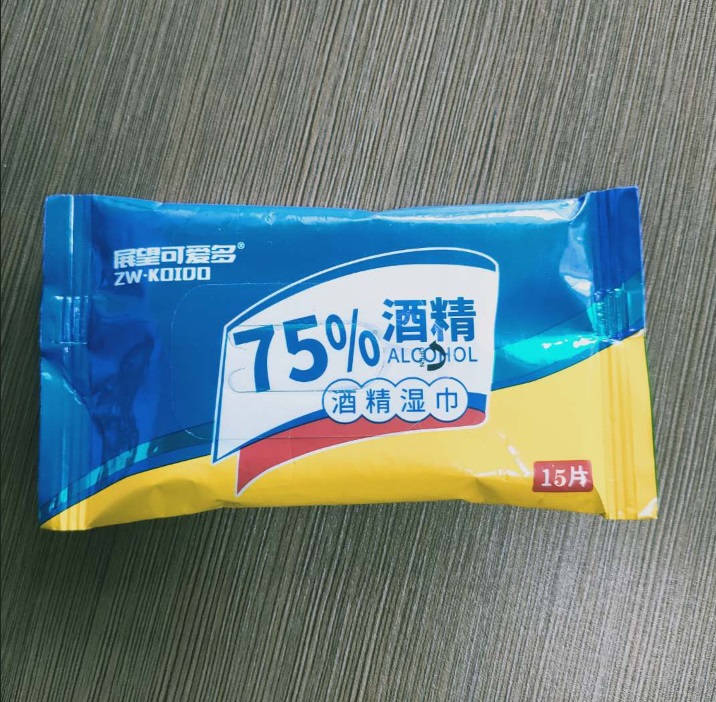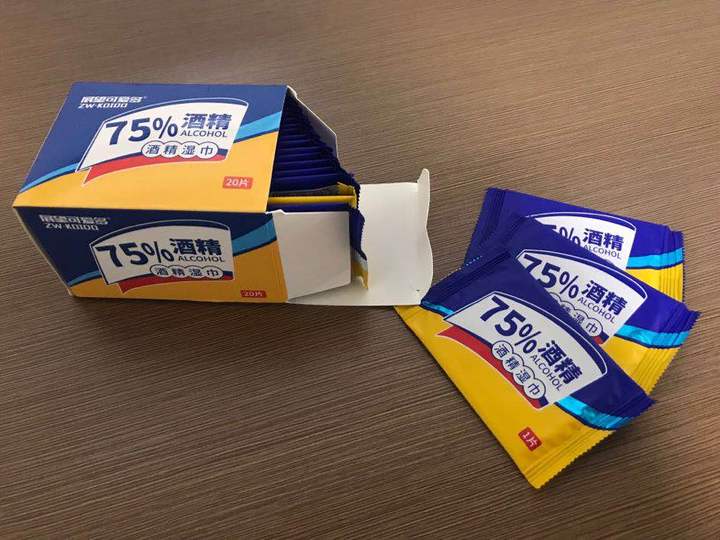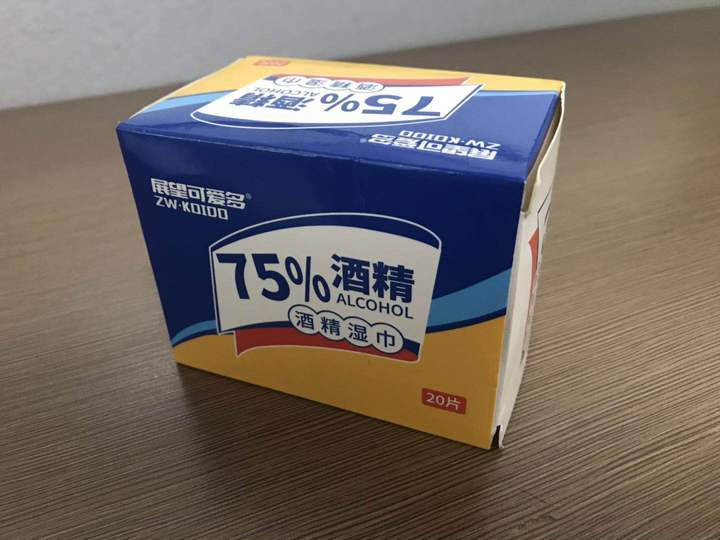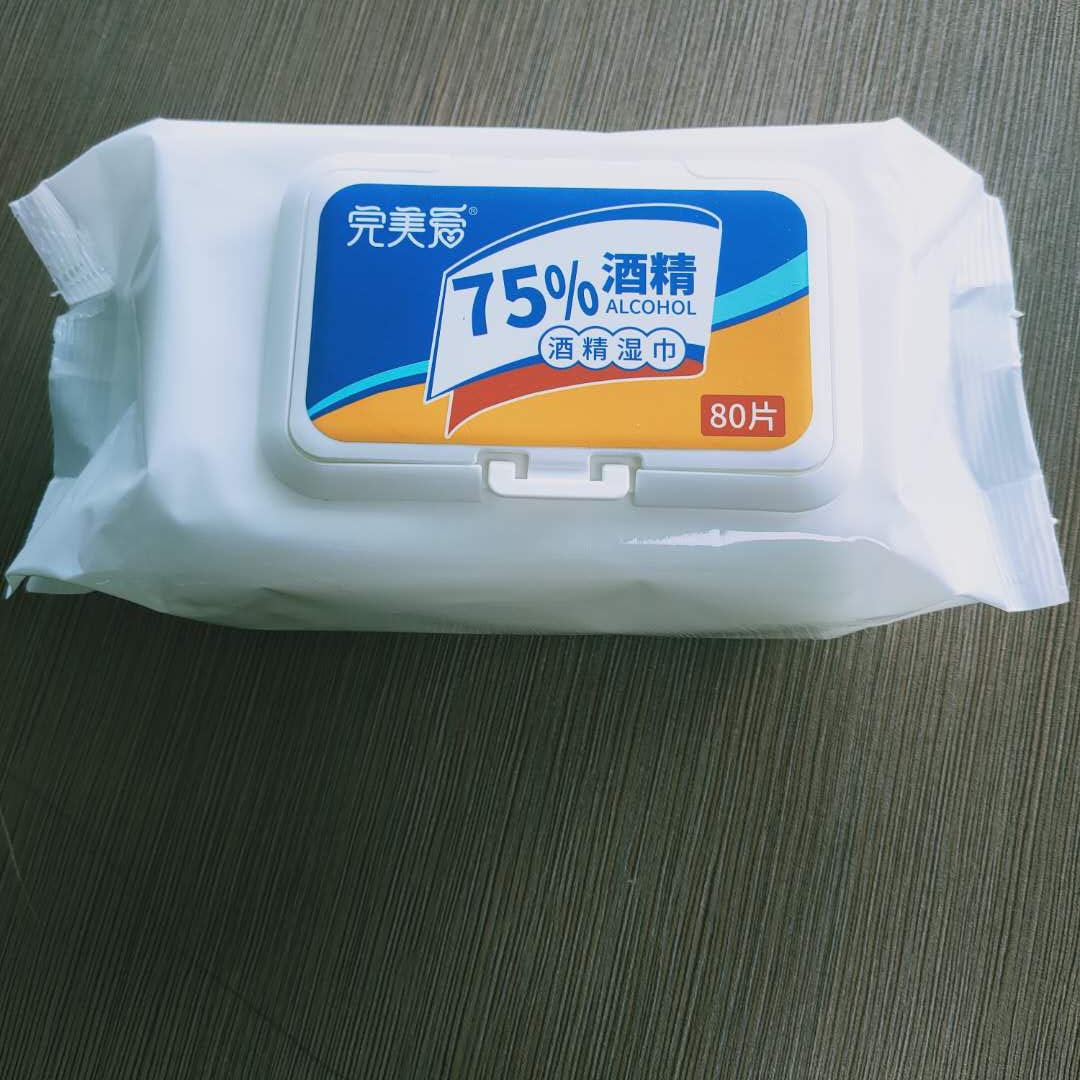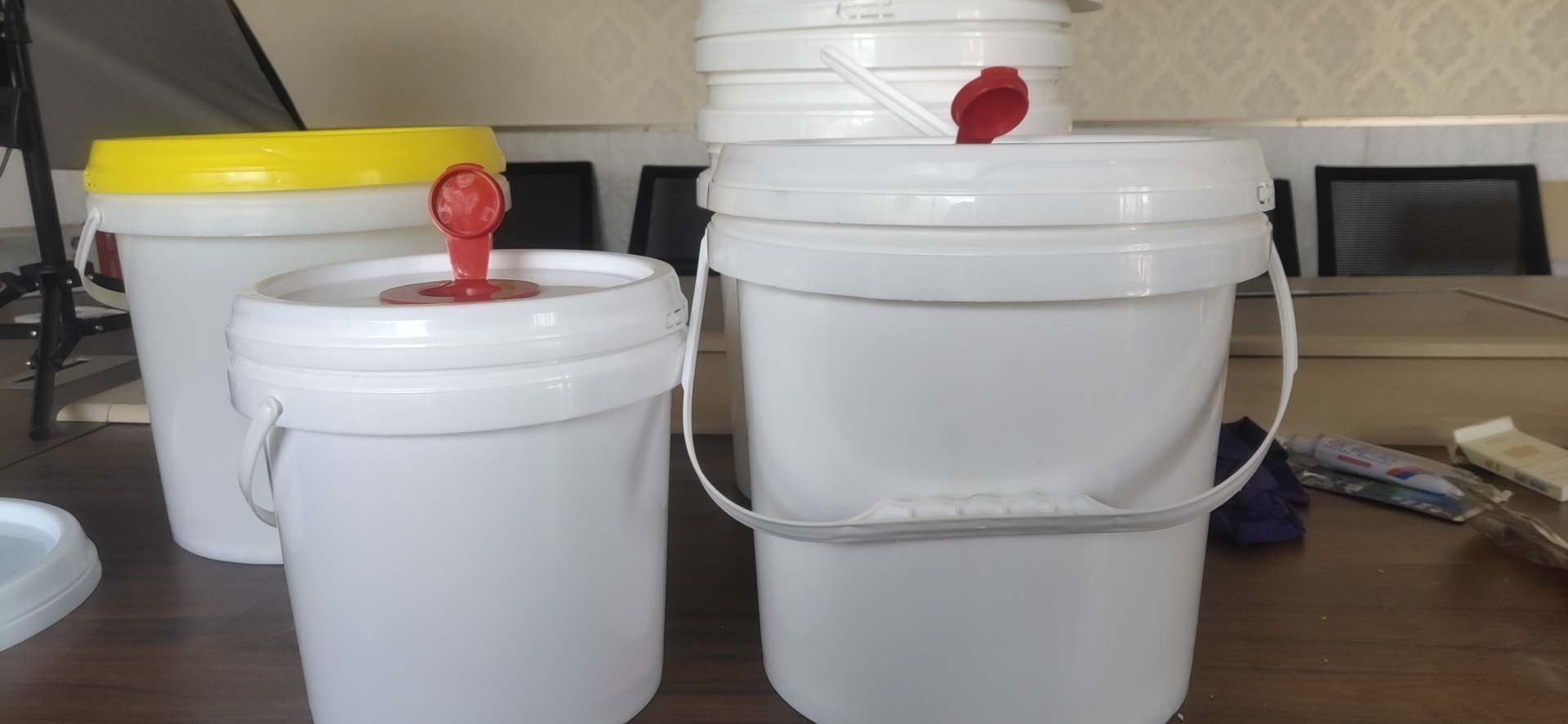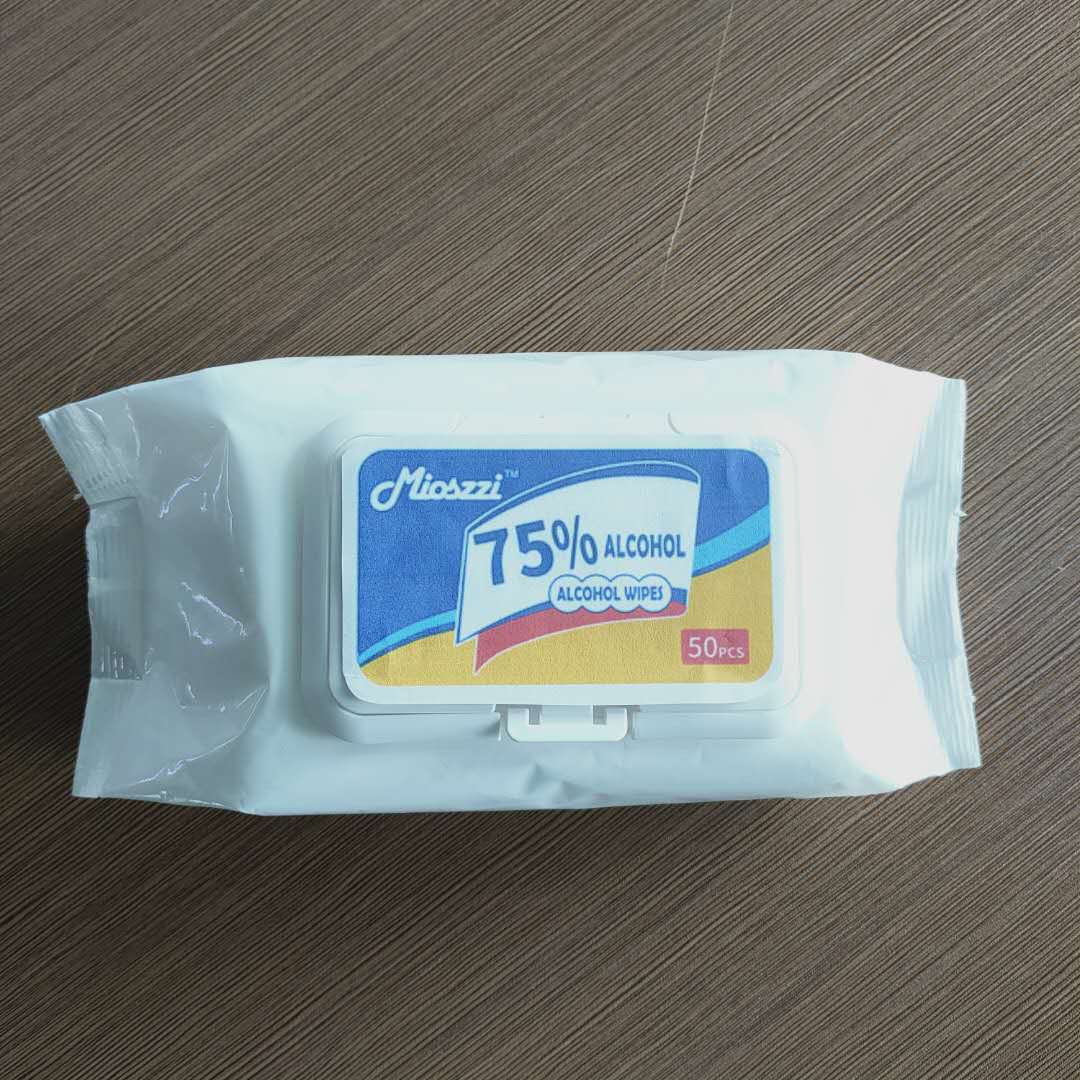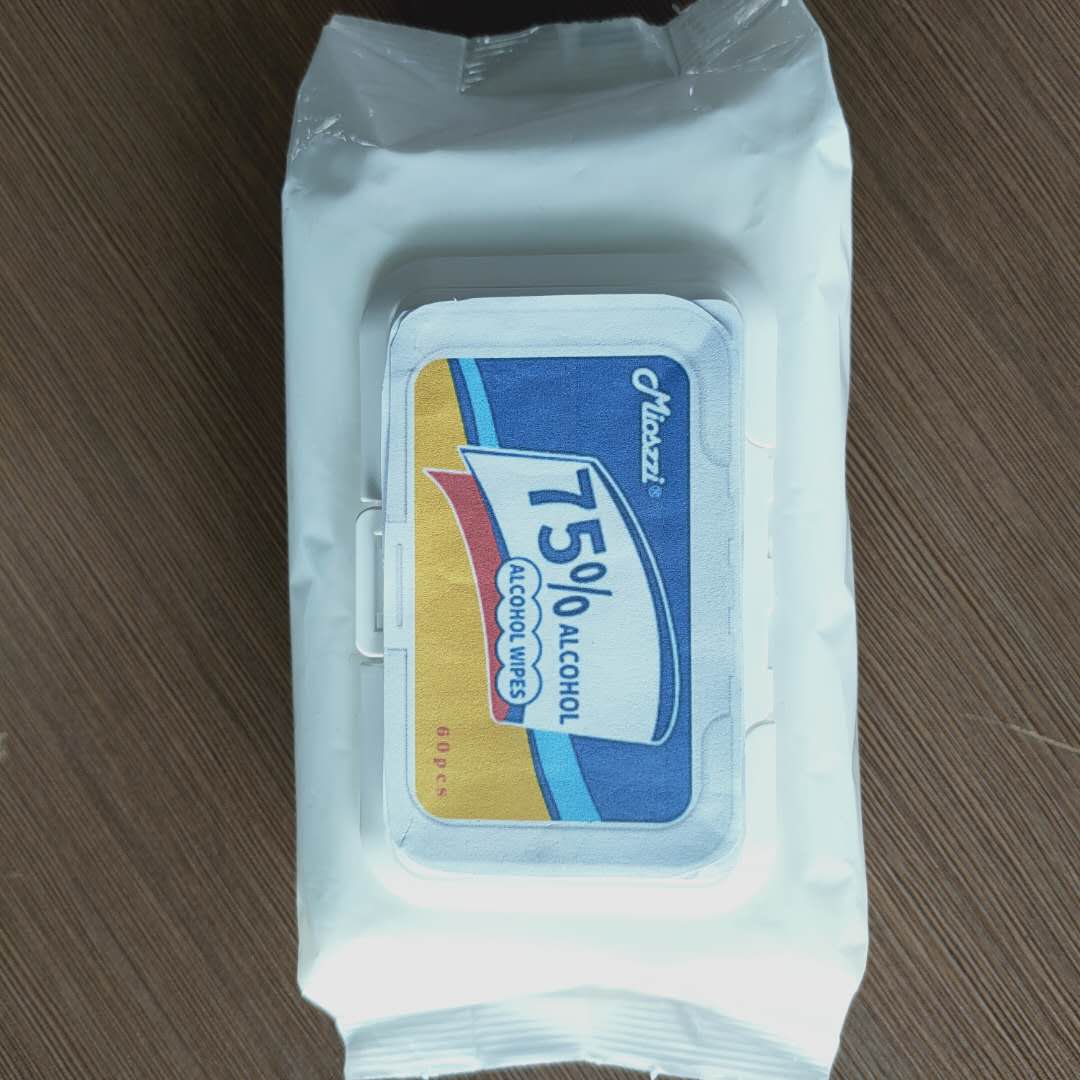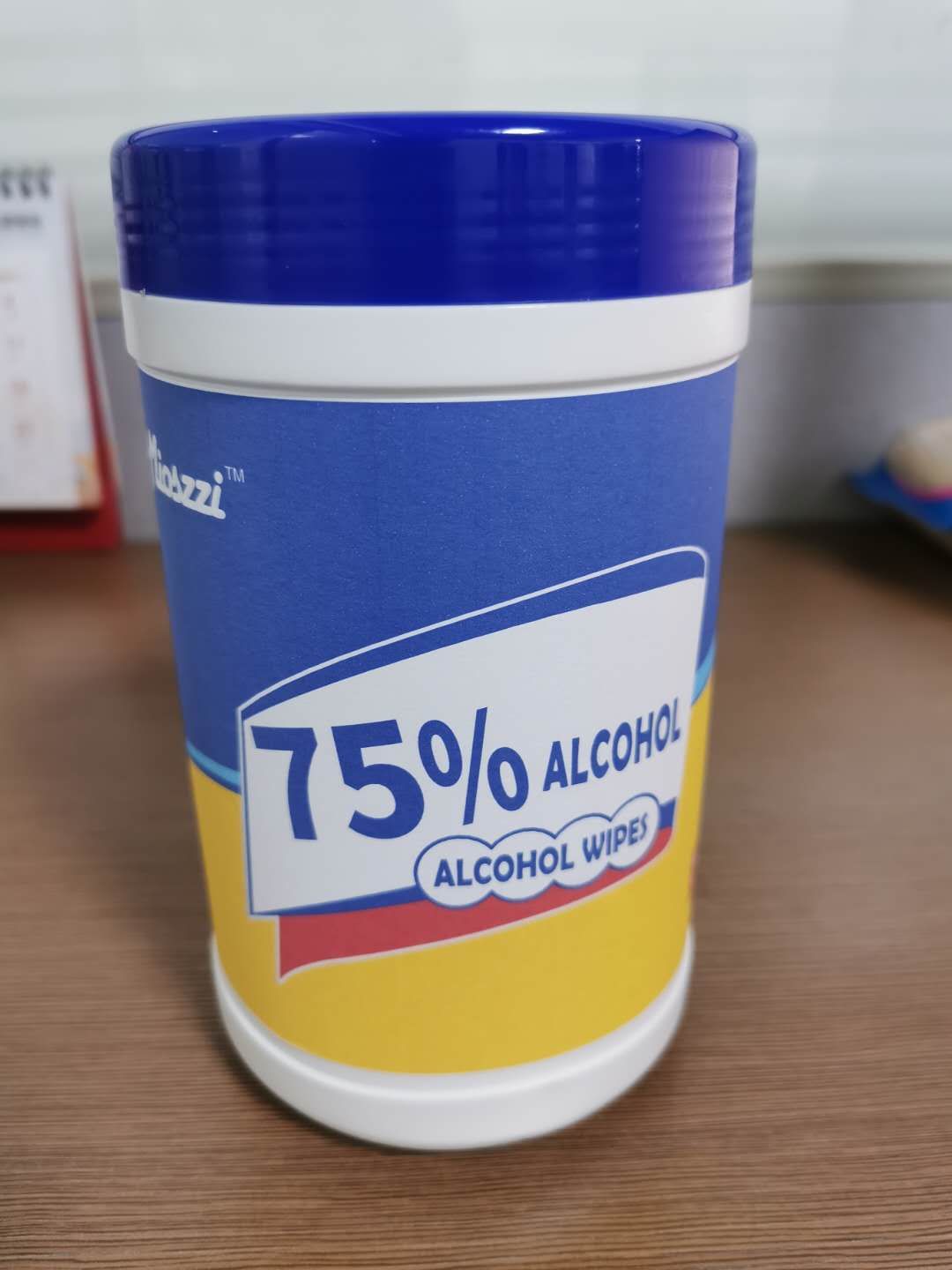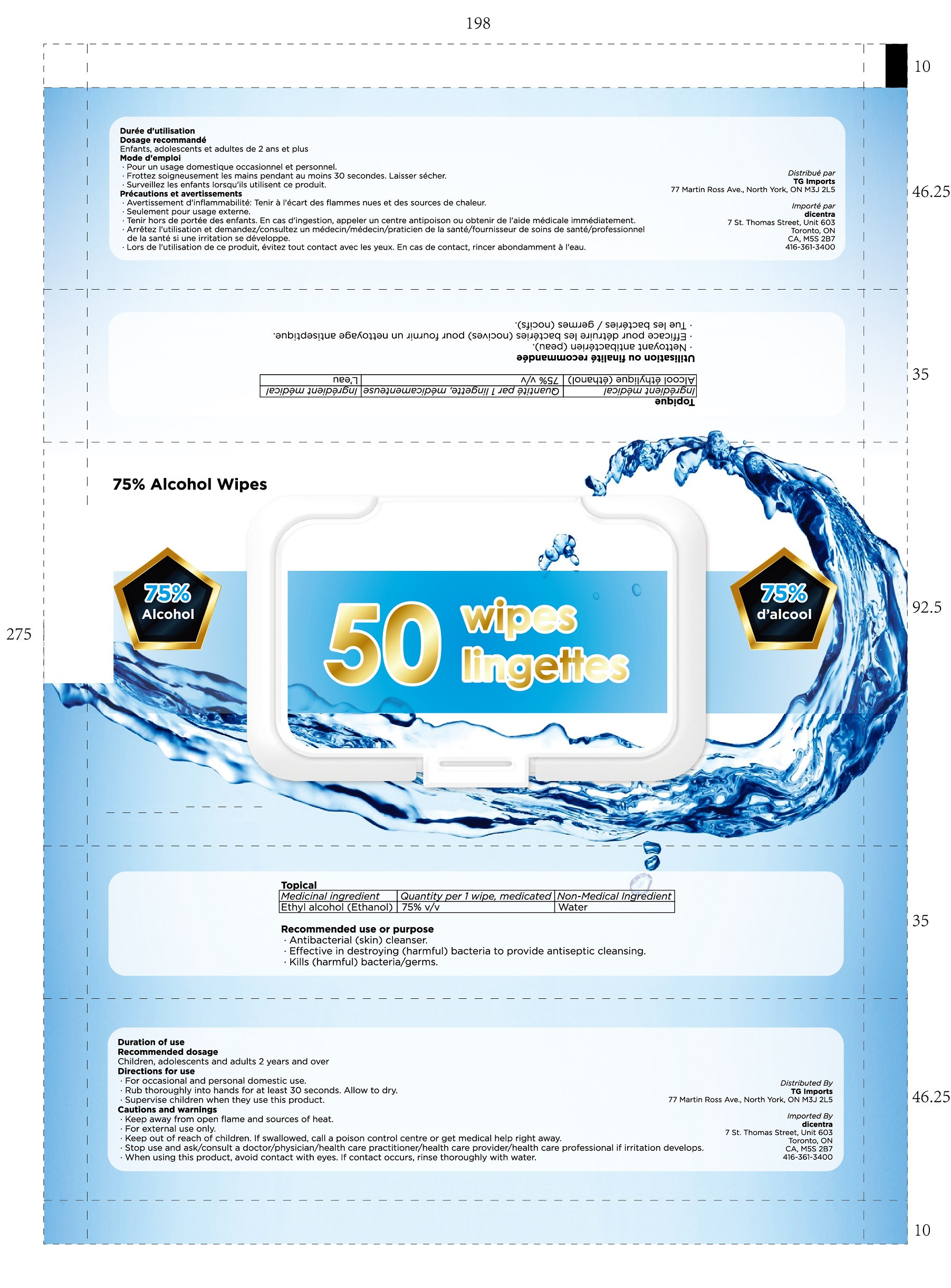 DRUG LABEL: alcohol wipes
NDC: 75269-013 | Form: CLOTH
Manufacturer: LINGHAI ZHANWANG BIOTECHNOLOGY CO.,LTD.
Category: otc | Type: HUMAN OTC DRUG LABEL
Date: 20241228

ACTIVE INGREDIENTS: ALCOHOL 75 mL/100 mL
INACTIVE INGREDIENTS: WATER

75269-013 alcohol wipes

Active ingredient(s)

Alcohol 75%

Purpose

Antiseptic

Warnings

Do not use if you are allergic to alcohol, avoid contact with eyes.

This product is disposable and cannot be reused.

This product contains alcohol, away from sources of ignition, and should only be used outside the skin to avoid contact with the eyes. Do not allow infants to come into contact alone to avoid accidental ingestion.

This product is insoluble in water, do no flush into the toilet.

Keep out of reach of children. If swallowed, get medical help right away.

Warnings

Keep out of reach of children. If swallowed, get medical help right away.

Other information

Storage Method: Store in a cool place to avoid volatilization.

Shelf Life: 2 years

Inactive ingredient(s)

Water

Usage

Open the sticker and then wipe.

Usage

Open the sticker and then wipe.

Medicinal ingredient

Ethyl alcohol (Ethanol) 75% v/v

Recommended use or purpose

Antibacterial (skin) cleanser.

Effective in destroying (harmful) bacteria to provide antiseptic cleansing.

Kills (harmful) bacteria/germs.

Cautions and warnings

Keep away from open flame and sources of heat.

For external use only.

Keep out of reach of children. If swallowed, call a poison control centre or get medical help right away.

Stop use and ask/consult a doctor/physician/health care practitioner/health care provider/health care professional if irritation develops.

When using this product, avoid contact with eyes. If contact occurs, rinse thoroughly with water.

Keep out of reach of children. If swallowed, call a poison control centre or get medical help right away.

Duration of use Recommended dosage

Children, adolescents and adults 2 years and over

Directions for use

For occasional and personal domestic use.

Rub thoroughly into hands for at least 30 seconds. Allow to dry.

Supervise children when they use this product.

Non-Medical Ingredient

Water

Package Label

ALCOHOL WIPES

10PCS

NDC: 75269-013-01

Package Label

ALCOHOL WIPES

1PCS

ALCOHOL WIPES

20 bags in a carton

NDC: 75269-013-02

Package Label

ALCOHOL WIPES

80PCS

NDC: 75269-013-03

Package Label

ALCOHOL WIPES

15PCS

NDC: 75269-013-04

Package Label

ALCOHOL WIPES

50PCS

NDC: 75269-013-05

Package Label

ALCOHOL WIPES

60PCS

NDC: 75269-013-06

Package Label

ALCOHOL WIPES

100PCS

NDC: 75269-013-07

Package Label

ALCOHOL WIPES

500PCS

NDC: 75269-013-08

Package Label

ALCOHOL WIPES

80 Sheets

NDC: 75269-013-09

PACKAGE LABEL

ALCOHOL WIPES

50 wipes

NDC: 75269-013-10